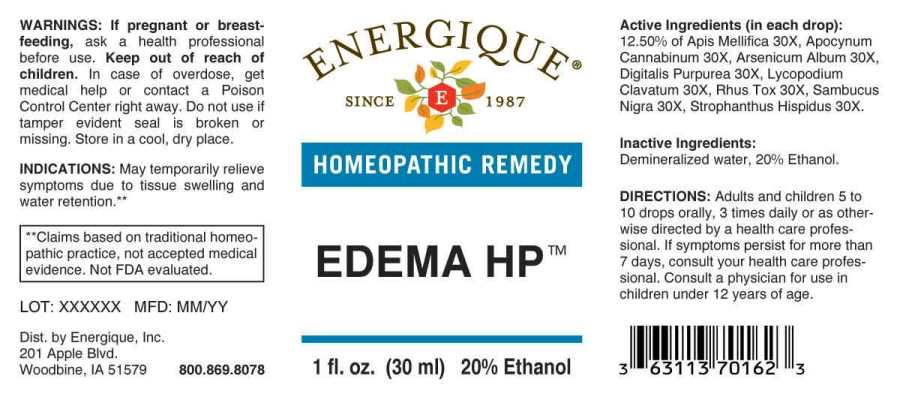 DRUG LABEL: Edema
NDC: 44911-0244 | Form: LIQUID
Manufacturer: Energique, Inc.
Category: homeopathic | Type: HUMAN OTC DRUG LABEL
Date: 20241024

ACTIVE INGREDIENTS: APIS MELLIFERA 30 [hp_X]/1 mL; APOCYNUM CANNABINUM ROOT 30 [hp_X]/1 mL; ARSENIC TRIOXIDE 30 [hp_X]/1 mL; DIGITALIS 30 [hp_X]/1 mL; LYCOPODIUM CLAVATUM SPORE 30 [hp_X]/1 mL; TOXICODENDRON PUBESCENS LEAF 30 [hp_X]/1 mL; SAMBUCUS NIGRA FLOWERING TOP 30 [hp_X]/1 mL; STROPHANTHUS HISPIDUS SEED 30 [hp_X]/1 mL
INACTIVE INGREDIENTS: WATER; ALCOHOL

DRUG FACTS:

ACTIVE INGREDIENTS:

(in each drop): 12.50% of Apis Mellifica 30X, Apocynum Cannabinum 30X, Arsenicum Album 30X, Digitalis Purpurea 30X, Lycopodium Clavatum 30X, Rhus Tox 30X, Sambucus Nigra 30X, Strophanthus Hispidus 30X.

INDICATIONS:

May temporarily relieve symptoms due to tissue swelling and water retention.**

**Claims based on traditional homeopathic practice, not accepted medical evidence. Not FDA evaluated.

WARNINGS:

If pregnant or breast-feeding, ask a health professional before use.

Keep out of reach of children. In case of overdose, get medical help or contact a Poison Control Center right away.

Do not use if tamper evident seal is broken or missing. Store in a cool, dry place.

Keep out of reach of children. In case of overdose, get medical help or contact a Poison Control Center right away.

DIRECTIONS:

Adults and children 5 to 10 drops orally, 3 times daily or as otherwise directed by a health care professional. If symptoms persist for more than 7 days, consult your health care professional. Consult a physician for use in children under 12 years of age.

INDICATIONS:

May temporarily relieve symptoms due to tissue swelling and water retention.**

**Claims based on traditional homeopathic practice, not accepted medical evidence. Not FDA evaluated.

INACTIVE INGREDIENTS:

Demineralized water, 20% Ethanol.

QUESTIONS:

Dist. by Energique, Inc.

201 Apple Blvd

Woodbine, IA 51579 800-869-8078

PACKAGE LABEL DISPLAY:

ENERGIQUE
SINCE 1987
HOMEOPATHIC REMEDY
EDEMA HP
1 fl. oz. (30 ml)